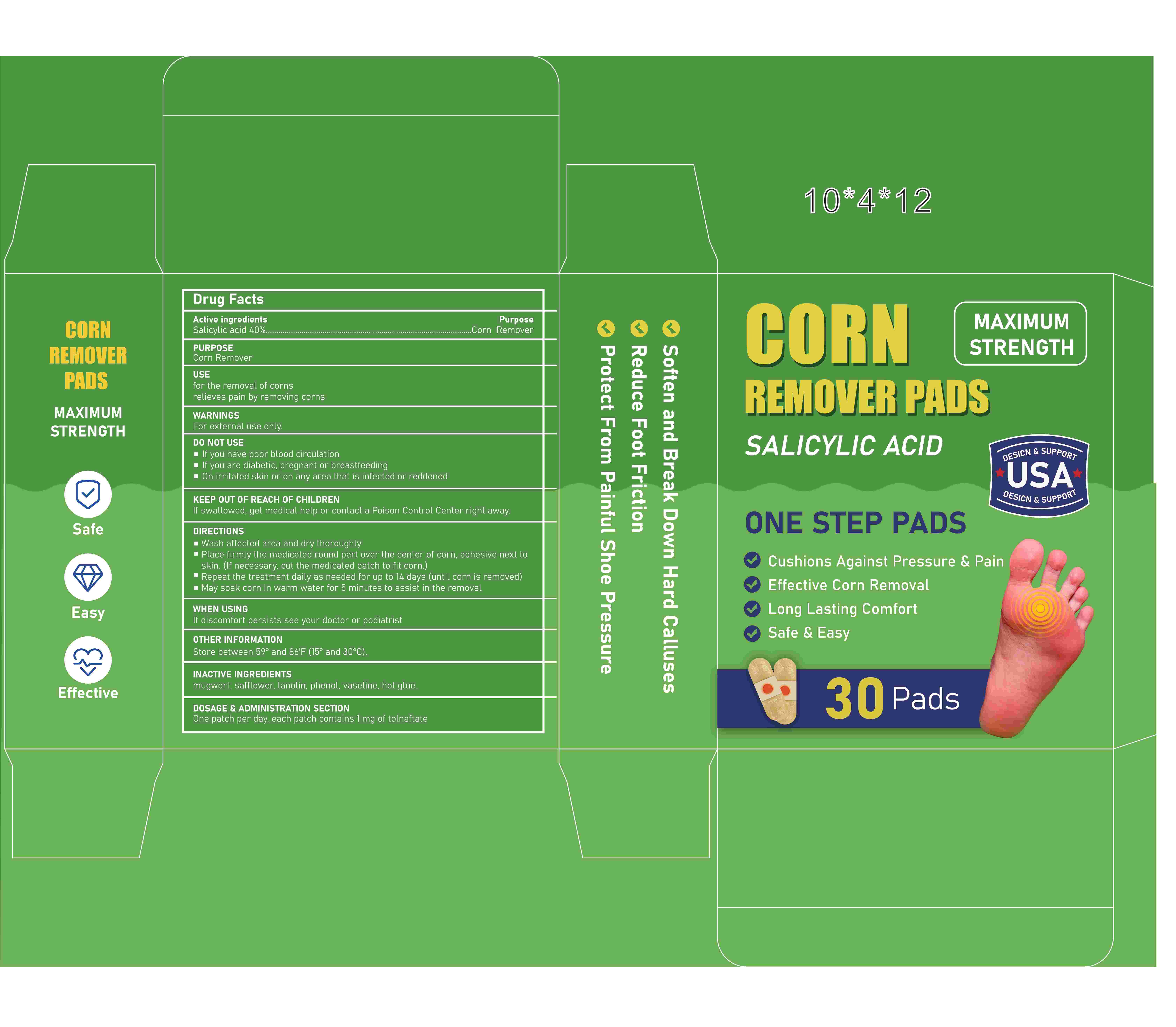 DRUG LABEL: Corn Remover Pads
NDC: 84023-111 | Form: PATCH
Manufacturer: Shenzhen Yangan Technology Co., Ltd.
Category: otc | Type: HUMAN OTC DRUG LABEL
Date: 20240927

ACTIVE INGREDIENTS: SALICYLIC ACID 40 mg/100 mg
INACTIVE INGREDIENTS: SAFFLOWER; PETROLATUM; LANOLIN; ARTEMISIA PRINCEPS LEAF

Corn Remover Pads

ACTIVE INGREDIENT

Salicylic acid 40%

PURPOSE

Corn Remover

WHEN USING

If discomfort persists see your doctor or podiatrist

WARNINGS

For external use only.

DO NOT USE

If you have poor blood circulation

If you are diabetic, pregnant or breastfeeding

On irritated skin or on any area that is infected or reddened

KEEP OUT OF REACH OF CHILDREN

DOSAGE AND ADMINISTRATION

One patch per day, each patch contains 1 mg of tollgate

INDICATIONS AND USAGE

Wash affected area and dry thoroughly

Place firmly the medicated round part over the center of corn, adhesive next to skin. (If necessary, cut the medicated patch to fit corn.)

Repeat the treatment daily as needed for up to 14 days (until corn is removed)

May soak corn in warm water for 5 minutes to assist in the removal

OTHER SAFETY INFORMATION

Store between 59°and 86'F (15°and 30°C).

INACTIVE INGREDIENT

mugwort, safflower, lanolin, phenol, vaseline, hot glue.

If discomfort persists see your doctor or podiatrist